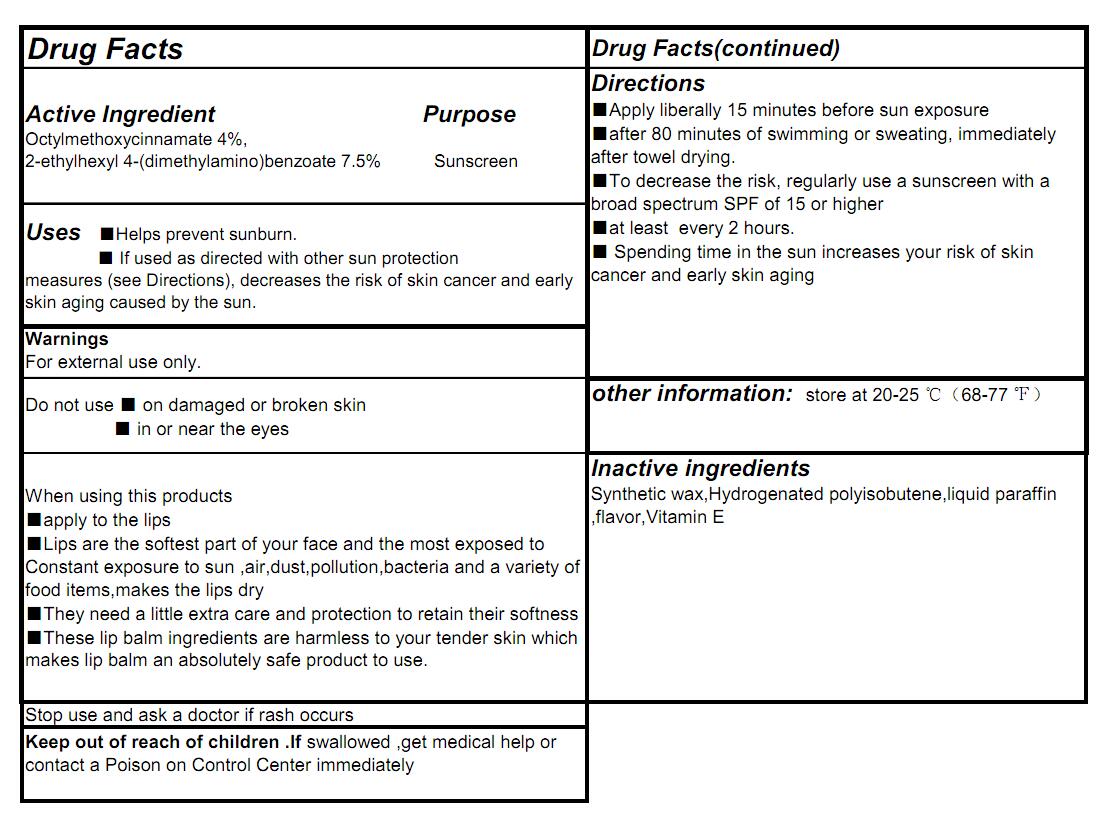 DRUG LABEL: sunscreen lip balm
NDC: 71011-002 | Form: STICK
Manufacturer: NingBo Huize Commodity Co.,Ltd.
Category: otc | Type: HUMAN OTC DRUG LABEL
Date: 20180106

ACTIVE INGREDIENTS: OCTINOXATE 4 g/100 g; PADIMATE O 7.5 g/100 g
INACTIVE INGREDIENTS: HYDROGENATED POLYBUTENE (1300 MW); PARAFFIN; VITAMIN A MYRISTATE; 1.ALPHA.,24S-DIHYDROXYVITAMIN D2; SYNTHETIC WAX (1200 MW)

sunscreen lip balm

Active Ingredient

Octylmethoxycinnamate 4%,
2-ethylhexyl 4-(dimethylamino)benzoate 7.5%

Purpose

Sunscreen

Use

Helps prevent sunburn.
If used as directed with other sun protection
measures (see Directions), decreases the risk of skin cancer and early skin aging caused by the sun.

WARNINGS

For external use only.
When using this products
■apply to the lips
■Lips are the softest part of your face and the most exposed to Constant exposure to sun ,air,dust,pollution,bacteria and a variety of food items,makes the lips dry
■They need a little extra care and protection to retain their softness
■These lip balm ingredients are harmless to your tender skin which makes lip balm an absolutely safe product to use.
Stop use and ask a doctor if rash occurs

Keep out of reach of children. If product is swallowed, get
medical help or contact a Poison Control Center right away.

Directions

■Apply liberally 15 minutes before sun exposure
■after 80 minutes of swimming or sweating, immediately after towel drying.
■To decrease the risk, regularly use a sunscreen with a broad spectrum SPF of 15 or higher
■at least every 2 hours.
■ Spending time in the sun increases your risk of skin cancer and early skin aging

Inactive ingredients

Synthetic wax,Hydrogenated polyisobutene,liquid paraffin ,flavor,Vitamin E